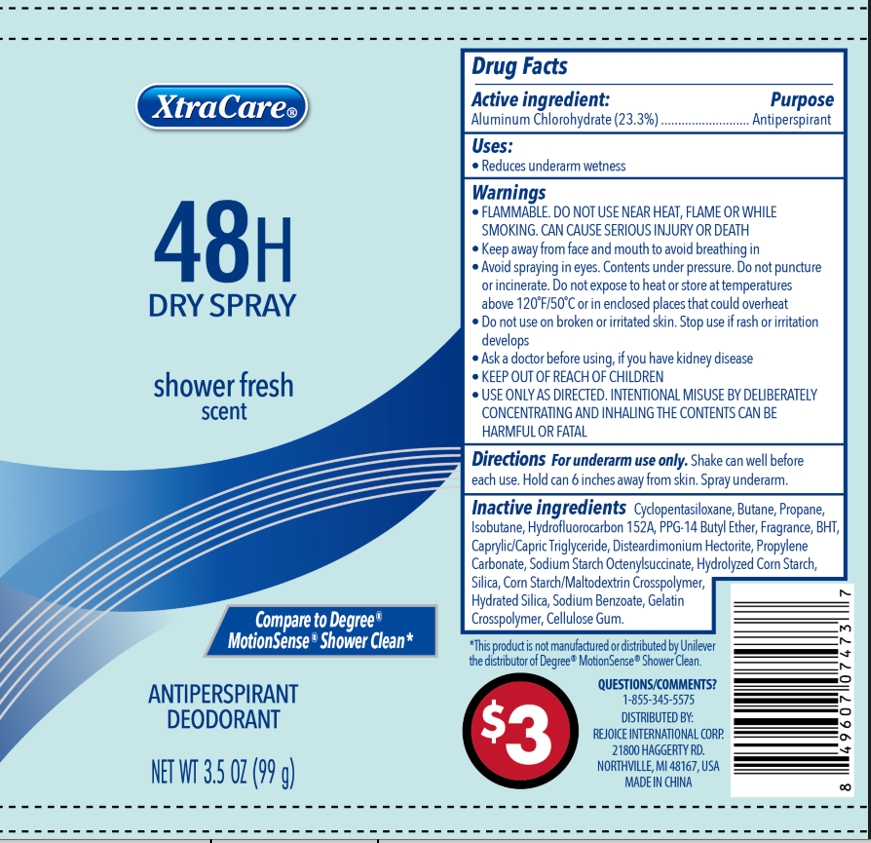 DRUG LABEL: Dry Shower Fresh 3.5oz
NDC: 57337-156 | Form: AEROSOL, SPRAY
Manufacturer: Rejoice International Corp.
Category: otc | Type: HUMAN OTC DRUG LABEL
Date: 20250128

ACTIVE INGREDIENTS: ALUMINUM CHLOROHYDRATE 23.3 g/100 g
INACTIVE INGREDIENTS: HYDRATED SILICA; SODIUM BENZOATE; ALUMINUM STARCH OCTENYLSUCCINATE; PROPYLENE CARBONATE; SILICON DIOXIDE; GELATIN, UNSPECIFIED; CORN SYRUP; STARCH, CORN; PROPANE; BUTYLATED HYDROXYTOLUENE; PPG-14 BUTYL ETHER; CARBOXYMETHYLCELLULOSE SODIUM, UNSPECIFIED FORM; MEDIUM-CHAIN TRIGLYCERIDES; CYCLOMETHICONE 5; BUTANE; DISTEARDIMONIUM HECTORITE; ISOBUTANE; 1,1-DIFLUOROETHANE

Dry Spray Shower Fresh 3.5oz

Active ingredient

Aluminum Chlorohydrate

Purpose

Antiperspirant

Uses

Reduces underarm wetness

Warnings

Flammable. Do not use near heat, flame or while smoking. Can cause serious injury or death

Do not use on broken or irritated skin. Stop use if rash or irritation develops.

When using

- Keep away from face and mouth to avoid breathing in
- Avoid spraying in eyes. Contents under pressure. Do not puncture or incinerate. Do not expose to heat or store at temperatures above 120ºF/50ºC or enclosed places that could overheat.
- USE ONLY AS DIRECTED. INTENTIONAL MISUSE BY DELIBERATELY CONCENTRATING AND INHALING THE CONTENT CAN BE HARMFUL OR FATAL.

Ask a doctor before using, if you have kidney disease.

Keep out of reach of children

Directions

For underarm use only. Shake can well before each use. Hold can 6 inches away from skin. Spray underarm.

Inactive ingredients

Cyclopentasiloxane; Butane; Propane; Isobutane; Hydrofluorocarbon 152A; PPG-14 Butyl Ether; Fragrance; BHT; Caprylic/Capric Triglyceride; Disteardimonium Hectorite; Propylene Carbonate; Sodium Starch Octenylsuccinate; Hydrolyzed Corn Starch; Silica; Corn Starch/Maltodextrin Crosspolymer; Hydrated Silica; Sodium Benzoate; Gelatin Crosspolymer; Cellulose Gum